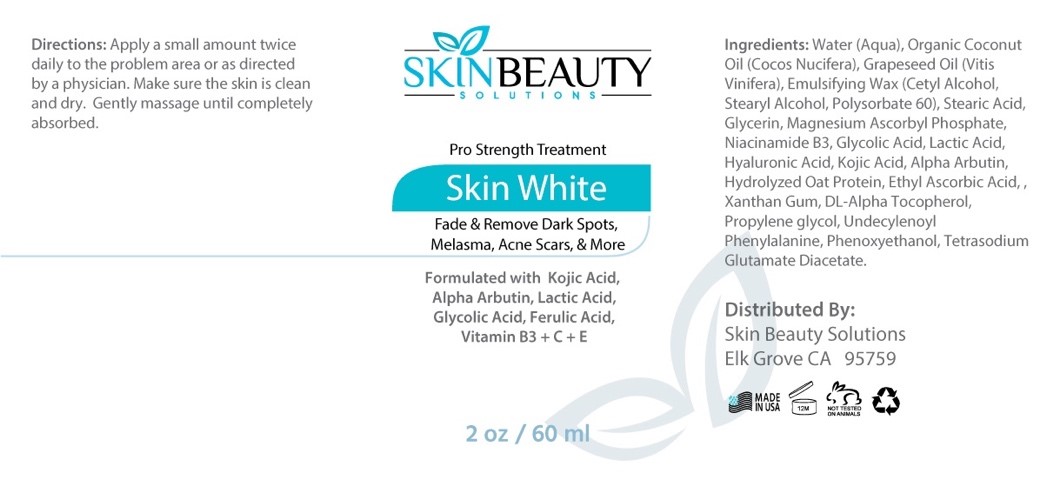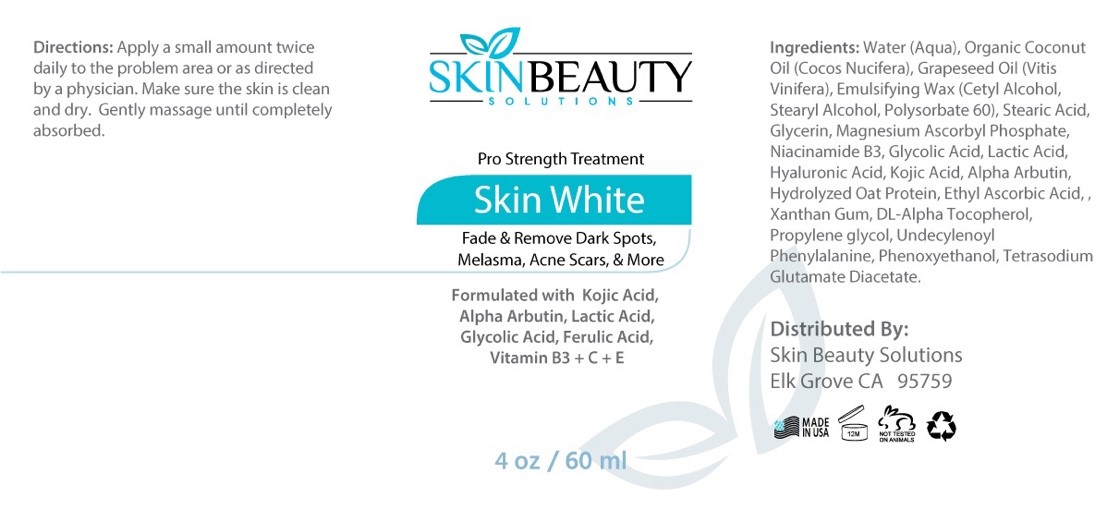 DRUG LABEL: Skin White Pro Strength Kojic and Hyaluronic Skin Lightening Serum
NDC: 84785-0010 | Form: SOLUTION
Manufacturer: Gazebo Wellness SKIN LLC
Category: otc | Type: HUMAN OTC DRUG LABEL
Date: 20241216

ACTIVE INGREDIENTS: HYALURONIC ACID 0.3 mg/30 mL; GLYCOLIC ACID 0.3 mg/30 mL; LACTIC ACID 0.3 mg/30 mL; NIACINAMIDE 0.3 mg/30 mL; KOJIC ACID 0.3 mg/30 mL; ALPHA-ARBUTIN 0.3 mg/30 mL; ASCORBIC ACID 0.3 mg/30 mL
INACTIVE INGREDIENTS: GLYCERIN; TETRASODIUM GLUTAMATE DIACETATE; PROPYLENE GLYCOL DIACETATE; MAGNESIUM ASCORBYL PHOSPHATE 0.3 mg/30 mL; COCONUT OIL; XANTHAN GUM; PHENOXYETHANOL; PHENYLALANINE; STEARIC ACID; .ALPHA.-TOCOPHEROL ACETATE, D- 0.3 mg/30 mL; WATER

DOSAGE AND ADMINISTRATION

Apply a small amount twice daily to the problem area or as directed by a physician. Make sure the skin is clean and dry. Gently massage until completely absorbed.

WARNINGS

Directions: Apply a small amount twice daily to the problem area or as directed by a physician. Make sure the skin is clean and dry. Gently massage until completely absorbed.

INACTIVE INGREDIENT

Inactive ingredients: Water, Organic Coconut Oil, Grapeseed Oil, Emulsifying Wax, Stearic Acid, Glycerin, Xanthan Gum, Propylene Glycol, Undecylenoyl Phenylalanine, Phenoxyethanol, Tetrasodium Glutamate Diacetate.

ACTIVE INGREDIENT

Active ingredients: Magnesium Ascorbyl Phosphate, Niacinamide B3, Glycolic Acid, Lactic Acid, Hyaluronic Acid, Kojic Acid, Alpha Arbutin, Hydrolyzed Oat Protein, Ethyl Ascorbic Acid, DL-Alpha Tocopherol (Vitamin E).

INDICATIONS AND USAGE

Directions: Apply a small amount twice daily to the problem area or as directed by a physician. Make sure the skin is clean and dry. Gently massage until completely absorbed.

keep out of reach of children

PURPOSE

Pro Strength Treatment
Skin White
Fade & Remove Dark Spots, Melasma, Acne Scars, & More
Formulated with Kojic Acid, Alpha Arbutin, Lactic Acid, Glycolic Acid, Ferulic Acid, Vitamin B3 + C + E

Distributed By: Skin Beauty Solutions Elk Grove CA 95759
MADE NUSA

PACKAGE LABEL

Content of labeling